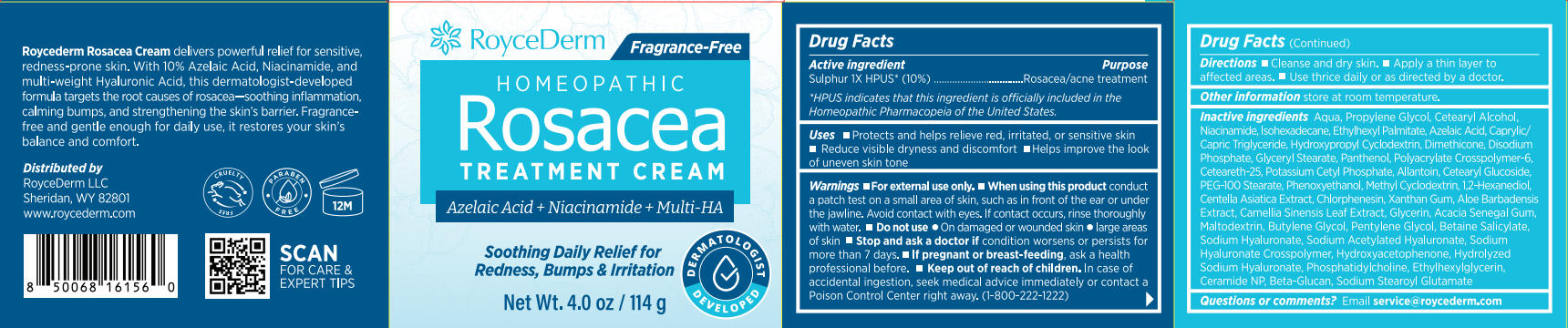 DRUG LABEL: RoyceDerm Rosacea Treatment Cream.
NDC: 85424-009 | Form: CREAM
Manufacturer: RoyceDerm LLC
Category: otc | Type: HUMAN OTC DRUG LABEL
Date: 20250904

ACTIVE INGREDIENTS: SULFUR 11.4 g/114 g
INACTIVE INGREDIENTS: CETEARYL ALCOHOL; TRANSFORMING GROWTH FACTOR BETA RECEPTOR TYPE 3; ETHYLHEXYL PALMITATE; DIMETHICONE; 1,2-HEXANEDIOL; LYSOPHOSPHATIDYLCHOLINE, SOYBEAN; CAMELLIA SINENSIS LEAF; HYDROXYACETOPHENONE; PENTYLENE GLYCOL; HYALURONATE SODIUM; PROPYLENE GLYCOL; ISOHEXADECANE; PANTHENOL; SODIUM ACETYLATED HYALURONATE; SODIUM STEAROYL GLUTAMATE; CERAMIDE NP; HYDROXYPROPYL BETADEX; ACACIA SENEGAL GUM; BETAINE SALICYLATE; ETHYLHEXYLGLYCERIN; AZELAIC ACID; DISODIUM PHOSPHATE; XANTHAN GUM; NIACINAMIDE; AQUA; CAPRYLIC/CAPRIC TRIGLYCERIDE; ALLANTOIN; CETEARYL GLUCOSIDE; PEG-100 STEARATE; CENTELLA ASIATICA TRITERPENOIDS; CHLORPHENESIN; GLYCERIN; BUTYLENE GLYCOL; POLYACRYLATE CROSSPOLYMER-6; CETEARETH-25; MALTODEXTRIN; PEG-9 DIGLYCIDYL ETHER/SODIUM HYALURONATE CROSSPOLYMER; GLYCERYL STEARATE; POTASSIUM CETYL PHOSPHATE; PHENOXYETHANOL; ALOE VERA WHOLE

Initial Drug Listing - RoyceDerm Rosacea Treatment Cream

ACTIVE INGREDIENT

Sulphur 1X HPUS*(10%)

PURPOSE

Rosacea/acne treatment

DOSAGE AND ADMINISTRATION

- Protects and helps relieve red, irritated, or sensitive skin
- Reduce visible dryness and discomfort
- Helps improve the lookuneven skin tone

WARNINGS

For external use only

WHEN USING

conduct a patch test on a small area of skin, such as in front of the ear or under the jawline. Avoid contact with eyes. lf contact occurs, rinse thoroughly with water.

DO NOT USE

- On damaged or wounded skin
- large areasof skin

ASK DOCTOR

condition worsens or persists for more than 7 days

PREGNANCY OR BREAST FEEDING

ask a health professional before

KEEP OUT OF REACH OF CHILDREN

In case of accidental ingestion, seek medical advice immediately or contact a Poison Control Center right away.(1-800-222-1222)

INDICATIONS AND USAGE

- Cleanse and dry skin.
- Apply a thin layer toaffected areas.
- Use thrice daily or as directed by a doctor.

OTHER SAFETY INFORMATION

store at room temperature.

INACTIVE INGREDIENT

Aqua, Propylene Glycol, Cetearyl Alcohol,Niacinamide, lsohexadecane, Ethylhexyl Palmitate, Azelaic Acid, Caprylic/Capric Triglyceride, Hydroxypropyl Cyclodextrin, Dimethicone, Disodium Phosphate, Glyceryl Stearate, Panthenol, Polyacrylate Crosspolymer-6, Ceteareth-25, Potassium Cetyl Phosphate, Allantoin, Cetearyl Glucoside.PEG-100 Stearate, Phenoxyethanol, Methyl Cyclodextrin, 1,2-Hexanediol,Centella Asiatica Extract, Chlorphenesin, Xanthan Gum, Aloe Barbadensis Extract, Camellia Sinensis Leaf Extract, Glycerin, Acacia Senegal Gum,Maltodextrin, Butylene Glycol, Pentylene Glycol, Betaine Salicylate,Sodium Hyaluronate, Sodium Acetylated Hyaluronate, Sodium Hyaluronate Crosspolymer, Hydroxyacetophenone, Hydrolyzed Sodium Hyaluronate, Phosphatidylcholine, Ethylhexylglycerin,Ceramide NP, Beta-Glucan, Sodium Stearoyl Glutamate

QUESTIONS

Email service@roycederm.com